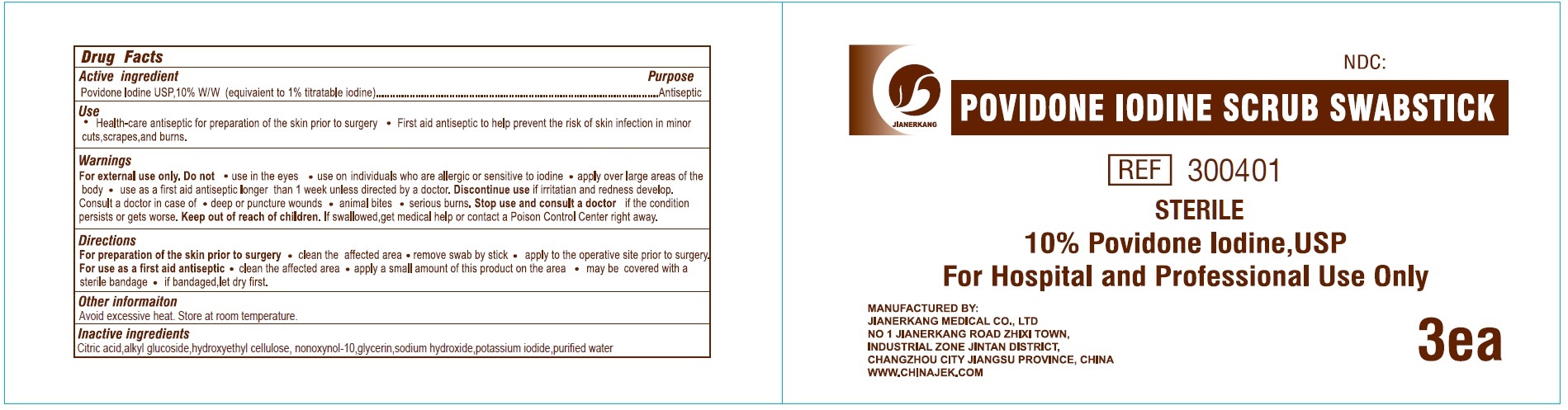 DRUG LABEL: POVIDONE IODINE SCRUB SWABSTICK 3s
NDC: 34645-0023 | Form: SWAB
Manufacturer: Jianerkang Medical Co., Ltd
Category: otc | Type: HUMAN OTC DRUG LABEL
Date: 20231023

ACTIVE INGREDIENTS: POVIDONE-IODINE 100 mg/1 mL
INACTIVE INGREDIENTS: CITRIC ACID MONOHYDRATE; HYDROXYETHYL CELLULOSE, UNSPECIFIED; NONOXYNOL-10; GLYCERIN; SODIUM HYDROXIDE; POTASSIUM IODIDE; WATER

POVIDONE IODINE SCRUB SWABSTICK 3's

Active ingredient

Povidone Iodine USP, 10% W/W (equivalent to 1% titratable iodine)

Purpose

Antiseptic

Use

- Health-care antiseptic for preparation of the skin prior to surgery
- First aid antiseptic to help prevent the risk of skin infection in minor cuts, scrapes, and burns.

Warnings

For external use only.

Do not

- use in the eyes
- use on individuals who are allergic or sensitive to iodine
- apply over large areas of the body
- use as a first aid antiseptic longer than 1 week unless directed by a doctor. if irritation and redness develop. Discontinue use

Consult a doctor in case of

- deep or puncture wounds
- animals bites
- serious burns.

Stop use and consult a doctor

- if the condition persists or gets worse

Keep out of reach of children.

If swallowed, get medical help or contact a Poison Control Center right away.

Directions

For preparation of the skin prior to surgery

For use as a first aid antiseptic

- clean the affected area
- remove swab by stick
- apply to the operative site prior to surgery.

- clean the affected area
- apply a small amount of this product on the area
- may be covered with a sterile bandage
- if benadaged, let dry first.

Other information

Avoid excessive heat. Store at room temperature.

Inactive ingredients

Citric acid, alkyl glucoside, hydroxyethyl cellulose, nonoxynol-10, glycerin, sodium hydroxide, potassium iodide, purified water